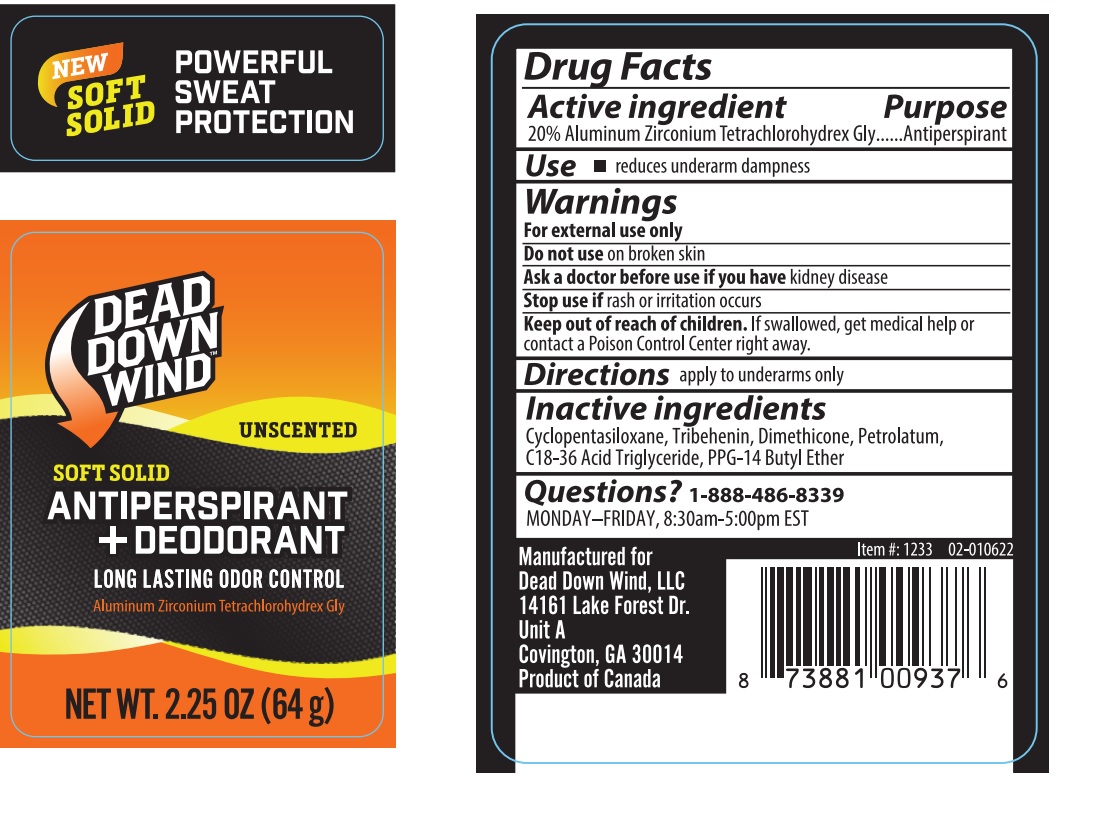 DRUG LABEL: Dead Down Wind Unscented Soft Solid Antiperspirant and Deodorant
NDC: 81502-001 | Form: STICK
Manufacturer: Dead Down Wind, LLC
Category: otc | Type: HUMAN OTC DRUG LABEL
Date: 20241223

ACTIVE INGREDIENTS: ALUMINUM ZIRCONIUM TETRACHLOROHYDREX GLY 12.8 g/64 g
INACTIVE INGREDIENTS: CYCLOMETHICONE 5; TRIBEHENIN; DIMETHICONE; PETROLATUM; C18-36 ACID TRIGLYCERIDE; PPG-14 BUTYL ETHER

Dead Down Wind Unscented Soft Solid Antiperspirant + Deodorant

Active ingredient

20% Aluminum Zirconium Tetrachlorohydrex Gly

Purpose

Antiperspirant

Use

- reduces underarm dampness

Warnings

For external use only

Do not useon broken skin

Ask a doctor before use if you havekidney disease

Stop use ifrash or irritation occurs

Keep out of reach of children.If swallowed, get medical help or contact a Poison Control Center right away.

Directions

apply to underarms only

Inactive ingredients

Cyclopentasiloxane, Tribehenin, Dimethicone, Petrolatum, C18-36 Acid Triglyceride, PPG-14 Butyl Ether

Questions?

1-888-486-8339

MONDAY-FRIDAY, 8:30am-5:00pm EST

NEW

SOFT SOLID

POWERFUL SWEAT PROTECTION

UNSCENTED

ANTIPERSPIRANT+DEODORANT

LONG LASTING ODOR CONTROL

Manufactured for
Dead Down Wind, LLC
14161 Lake Forest Dr.
Unit A
Covington, GA 30014
Product of Canada